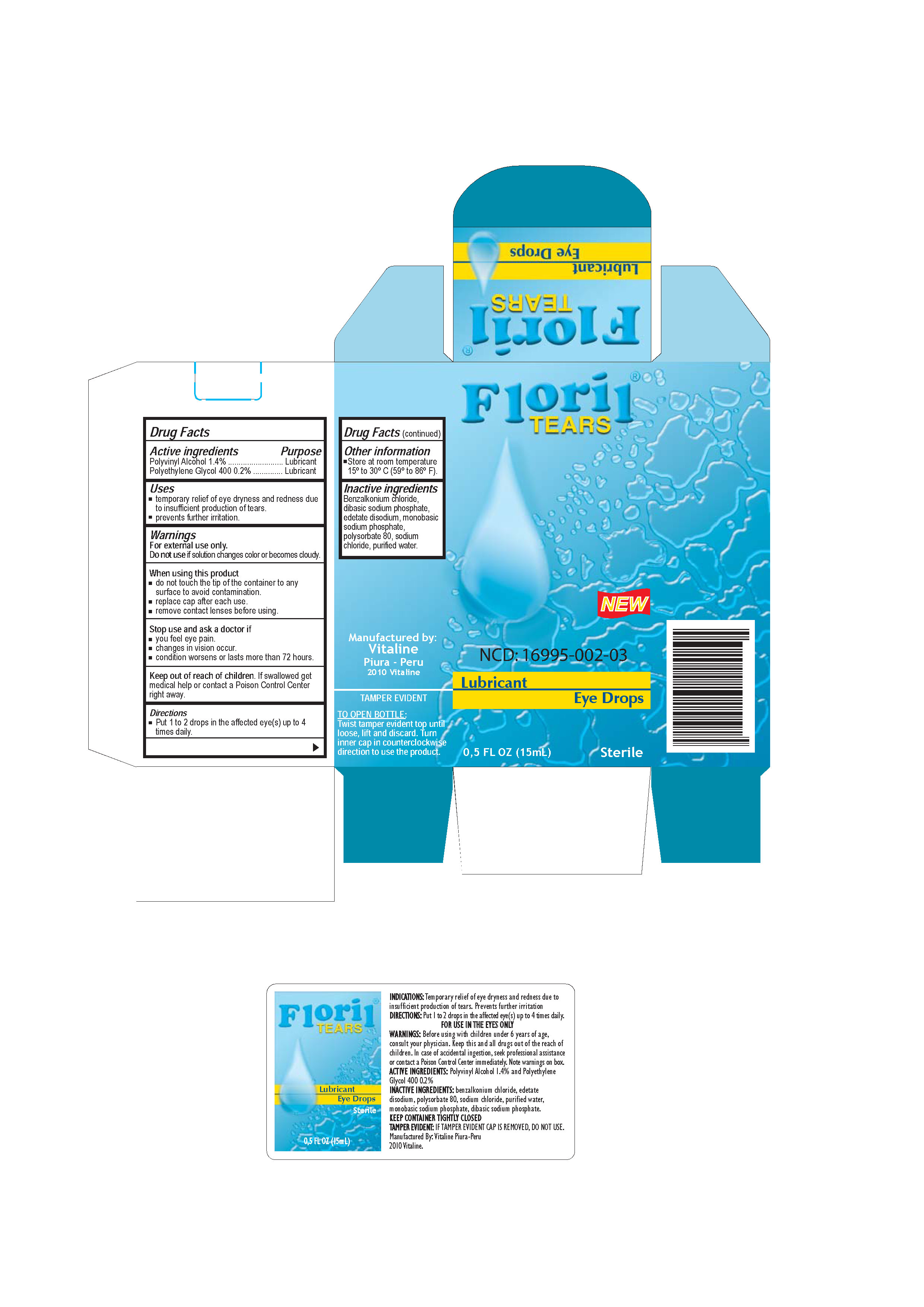 DRUG LABEL: FLORIL TEARS
NDC: 16995-004 | Form: SOLUTION/ DROPS
Manufacturer: VITALINE S.A.C.
Category: otc | Type: HUMAN OTC DRUG LABEL
Date: 20100622

ACTIVE INGREDIENTS: POLYVINYL ALCOHOL 14 mg/1 mL
INACTIVE INGREDIENTS: WATER; POLYETHYLENE GLYCOL 300 2 mg/1 mL

Active ingredients Purpose

Polyvinyl Alcohol 1,4% Lubricant

When using this product

- do not touch the tip of the container to any surface to avoid contamination
- replace cap after each use
- remove contact lenses before using

Stop use and ask a doctor if

- You feel eye pain
- changes in vision occur
- condition worsens or lasts more than 72 hours

Keep our of reach of children.

If swallowed get medical help or contact a Poison Control Center right away.

Inactive ingredients

Benzalkonium chloride, dibasic sodium phosphate, edetate disodium, monobasic sodium phosphate, polysorbate 80, sodium chloride, polyethylene glycol 300, purified water.

WARNINGS

For external use only.

Do not use if the solution changes color or become cloudy.

Directions

- Put 1 to 2 drops in the affected eyes up to times daily.

Other information

Enter section text here

Uses

- temporary relief of eye dryness and redness due to insufficient production of tears.
- prevents further irritation.

PACKAGE LABEL

Enter section text here